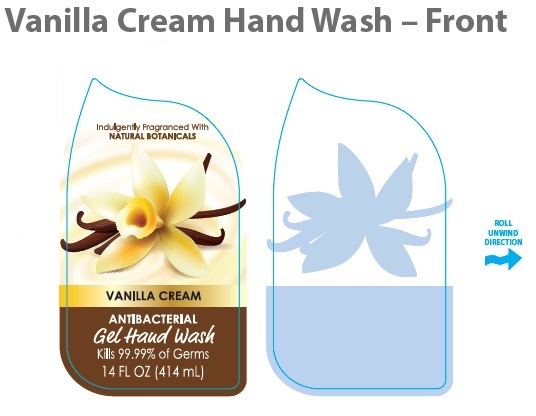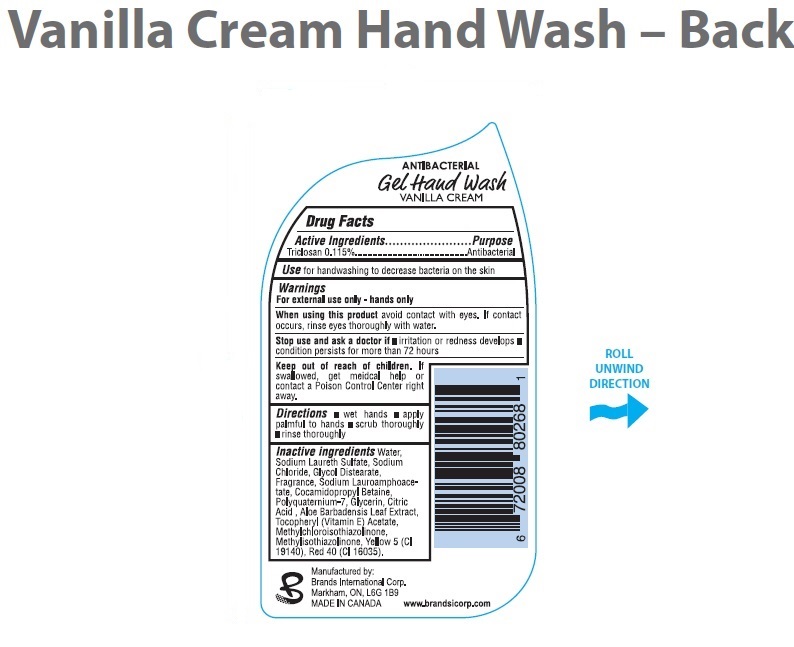 DRUG LABEL: Vanilla Cream
NDC: 50157-113 | Form: LIQUID
Manufacturer: Brands International
Category: otc | Type: HUMAN OTC DRUG LABEL
Date: 20151031

ACTIVE INGREDIENTS: TRICLOSAN 1.15 mg/1 mL
INACTIVE INGREDIENTS: WATER; SODIUM LAURETH SULFATE; SODIUM CHLORIDE; COCAMIDOPROPYL BETAINE; POLYQUATERNIUM-7 (70/30 ACRYLAMIDE/DADMAC; 1600 KD); SODIUM LAUROAMPHOACETATE; D&C RED NO. 33; ALPHA-TOCOPHEROL ACETATE; METHYLCHLOROISOTHIAZOLINONE; METHYLISOTHIAZOLINONE; FD&C YELLOW NO. 5; GLYCOL DISTEARATE; GLYCERIN; CITRIC ACID MONOHYDRATE; ALOE VERA LEAF

Vanilla Cream Antibacterial Gel Hand Wash

Drug Facts

Active Ingredients

Triclosan 0.115%

Purpose

Antibacterial

Uses

for handwashing to decrease bacteria on the skin

Warnings

For external use only.

Stop use and ask a doctor if irritation or redness develops.

When using this product do not get into eyes. If contact occurs, rinse eye thoroughly with water.

Keep out of reach of children. If swallowed, get medical help or contact a Poison Control Center right away.

Directions

- wet hands
- apply palmful to hands
- scrub thoroughly
- rinse

Inactive ingredients

Water, Sodium Laureth Sulfate, Sodium Chloride, DMDM Hydantoin, Citric Acid, Fragrance, EDTA, Yellow # 5, Red # 33

Package Label

Vanilla Cream Hand Wash

Antibacterial

Refill
14 oz / 414ml
Hand Soap